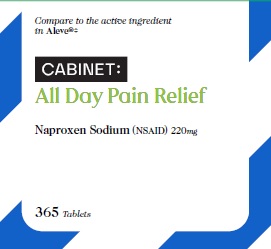 DRUG LABEL: NAPROXEN SODIUM
NDC: 68210-4096 | Form: TABLET, FILM COATED, EXTENDED RELEASE
Manufacturer: SPIRIT PHARMACEUTICALS,LLC
Category: otc | Type: HUMAN OTC DRUG LABEL
Date: 20241230

ACTIVE INGREDIENTS: NAPROXEN SODIUM 220 mg/1 1
INACTIVE INGREDIENTS: FD&C BLUE NO. 2; HYPROMELLOSES; STARCH, CORN; MICROCRYSTALLINE CELLULOSE; POLYETHYLENE GLYCOL, UNSPECIFIED; POVIDONE K30; SODIUM STARCH GLYCOLATE TYPE A POTATO; STEARIC ACID; TITANIUM DIOXIDE

NAPROXEN SODIUM TABLETS, USP 220 mg

Drug Facts

ACTIVE INGREDIENT

Naproxen sodium 220 mg

(naproxen 200 mg) (NSAID)*

*nonsteroidal anti-inflammatory drug

PURPOSE

Pain reliever/

fever reducer

Uses

- temporarily relieves minor aches and pain due to :
- backache
- headache
- menstrul cramps
- minor pain of arthritis
- muscular aches
- the common cold
- toothache
- temporarily reduces fever

Warnings

Allergy alert

Naproxen sodium may cause a severe allergic reaction, especially in people allergic to aspirin. Symptoms may include:

- asthma (wheezing)
- blisters
- facial swelling
- hives
- rash
- shock
- skin reddening

If an allergic reaction occurs, stop use and seek medical help right away.

Stomach bleeding warning

This product contains a non steroidal anti-inflammatory drug(NSAID), which may cause severe stomach bleeding. The chance is higher if you:

- are age 60 or older
- have had stomach ulcers or bleeding problems
- take a blood thinning(anticoagulant) or steroid drug
- take other drugs containing prescription or nonprescription NSAIDs(aspirin, ibuprofen, naproxen, or others)
- have 3 or more alcoholic drinks every day while using this product
- take more or for a longer time than directed

Heart attack and stroke warning

NSAID's except aspirin increases the risk of heart attack, heart failure and stroke. These can be fatal. The risk is higher if you use more than directed or for longer than directed.

Do not use

- if you have ever had an allergic reaction to any other pain reliever / fever reducer
- right before or after surgery

Ask a doctor before use if

- the stomach bleeding warning applies to you
- you have a history of stomach problems,such as a heartburn
- you have a high blood pressure, heart disease, liver cirrhosis or kidney disease
- you are taking a diuretic
- you have problems or serious side effects taking pain relievers or fever reducers
- you have asthma

Ask a doctor or pharmacist before use if you are

- under a doctor 's care for any serious conditions
- taking any other drug

When using this product

- take with food or milk if stomach upset occurs
- the risk of heart attack or stroke may increase if you use more than directed or for longer than directed

Stop use and ask a doctor if

- you experience any of following sign of stomach bleeding:
- feel faint
- vomit blood
- have bloody or black stools
- have stomach pain that does not get better
- pain gets worse or lasts more than 10 days
- fever gets worse or lasts more than 3 days
- you have difficulty swallowing
- it feel like the pill is stuck in your throat
- redness or swelling is present in the painful area
- any new symptoms appear

PREGNANCY OR BREAST FEEDING

If pregnant or breast feeding, ask a health profession before use. It is especially important not to use naproxen sodium during the last 3 months of pregnancy unless definitely directed to do so by a doctor because it may cause problems in the unborn child or complication during the delivery.

Keep out of reach of children. In case of overdose, get medical help or contact a position control center right away (1-800-222-1222)

Directions

- do not take more than directed
- the smallest effective dose should be used
- drink a full glass of water with each dose
Adults and Children 12 years and older: | - take one tablet every 8 to 12 hours while symptoms last - for the first dose you may take within the first hour - do not exceed 2 tablets in any 8 to 12 hours period - do not exceed 3 tablets in 24 hour period
Children under 12 years: | - Ask a doctor

Other information

- each tablet contains: sodium 20 mg
- store between 20°-25°C(68-77°F). Avoid high humidity and excessive heat above 40°C(104°F)

Inactive ingredients

Colloidal silicon dioxide*, croscarmellose sodium*, FD&C Blue#2 lake, hypromellose, magnesium stearate*, maize starch*, microcrystalline cellulose, polyethylene glycol, povidone, sodium starch glycolate*, stearic acid*, titanium dioxide.

*contains one or more of these ingredients

Questions or comments?

1-888-333-9792

PRINCIPAL DISPLAY PANEL

CABINET

NAPROXEN SODIUM TABLETS, USP 220 mg

PAIN RELIEVER/FEVER REDUCER (NSAID)